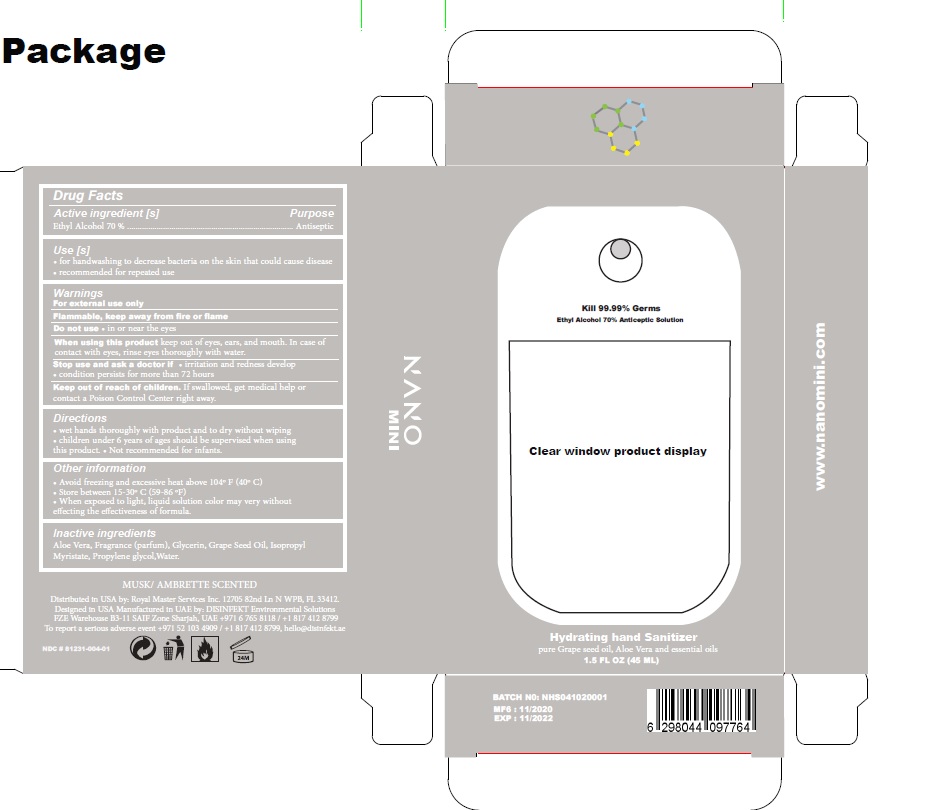 DRUG LABEL: NANO MINI I DO hand sanitizer
NDC: 81231-004 | Form: LIQUID
Manufacturer: DISINFEKT ENVIRONMENTAL SOLUTIONS FZE
Category: otc | Type: HUMAN OTC DRUG LABEL
Date: 20201218

ACTIVE INGREDIENTS: ALCOHOL 70 mL/100 mL
INACTIVE INGREDIENTS: ALOE VERA WHOLE; GLYCERIN; GRAPE SEED OIL; ISOPROPYL MYRISTATE; PROPYLENE GLYCOL; WATER

NANO MINI I DO

Active Ingredient

Ethyl Alcohol 70%

Purpose

Antiseptic.

Use [s]

- for handwashing to decrease bacteria on the skin that could cause disease.
- recommended for repeated use.

Warnings

- For external use only
- Flammable, keep away from fire or flame
- Do not use in or near the eyes

When using this product keep out of eyes, ears, and mouth.

- In case of contact with eyes, rinse eyes thoroughly with water rinse eyes thoroughly with water

Stop use and ask a doctor if

- irritation and redness develop.
- condition persists for more than 72 hours.

Keep out of reach of children.

If swallowed, get medical help or contact a Poison Control Center right away.

Directions

- wet hands thoroughly with product and to dry without wiping

• children under 6 years of ages should be supervised when using this product.

• Not recommended for infants.

Other information

- Avoid freezing and excessive heat above 104º F (40º C).
- Store between 15-30º C (59-86 ºF)
- When exposed to light, liquid solution color may very without effecting the effectiveness of formula.

Inactive ingredients

Aloe Vera, Fragrance (parfum), Glycerin, Grape Seed Oil, Isopropyl Myristate, Propylene glycol, Water